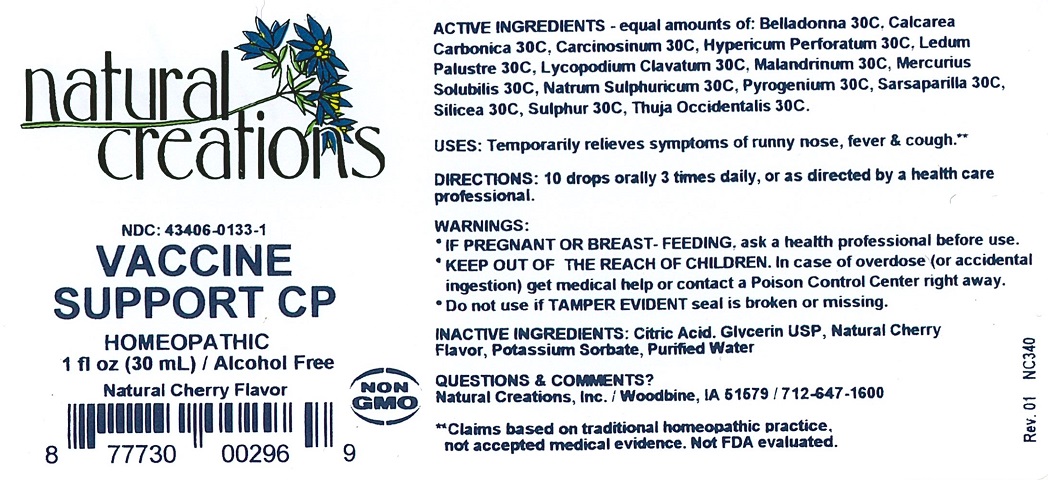 DRUG LABEL: Vaccine Support CP
NDC: 43406-0133 | Form: LIQUID
Manufacturer: Natural Creations, Inc
Category: homeopathic | Type: HUMAN OTC DRUG LABEL
Date: 20251218

ACTIVE INGREDIENTS: ATROPA BELLADONNA 30 [hp_C]/1 mL; OYSTER SHELL CALCIUM CARBONATE, CRUDE 30 [hp_C]/1 mL; HUMAN BREAST TUMOR CELL 30 [hp_C]/1 mL; HYPERICUM PERFORATUM WHOLE 30 [hp_C]/1 mL; RHODODENDRON TOMENTOSUM LEAFY TWIG 30 [hp_C]/1 mL; LYCOPODIUM CLAVATUM SPORE 30 [hp_C]/1 mL; MERCURIUS SOLUBILIS 30 [hp_C]/1 mL; SODIUM SULFATE 30 [hp_C]/1 mL; RANCID BEEF 30 [hp_C]/1 mL; SMILAX ORNATA ROOT 30 [hp_C]/1 mL; SILICON DIOXIDE 30 [hp_C]/1 mL; SULFUR 30 [hp_C]/1 mL; THUJA OCCIDENTALIS LEAFY TWIG 30 [hp_C]/1 mL
INACTIVE INGREDIENTS: CITRIC ACID MONOHYDRATE; GLYCERIN; POTASSIUM SORBATE; WATER

Vaccine Support CP

ACTIVE INGREDIENT

ACTIVE INGREDIENTS - equal amounts of: Belladonna 30C, Calcarea Carbonica 30C, Carcinosinum 30C, Hypericum Perforatum 30C, Ledum Palustre 30C, Lycopodium Clavatum 30C, Malandrinum 30C, Mercurius Solubilis 30C, Natrum Sulphuricum 30C, Pyrogenium 30C, Sarsaparilla 30C, Silicea 30C, Sulphur 30C, Thuja Occidentalis 30C

INDICATIONS AND USAGE

USES: Temporarily relieves symptoms of runny nose, fever & cough.**

PURPOSE

USES: Temporarily relieves symptoms of runny nose, fever & cough.**

DOSAGE AND ADMINISTRATION

DIRECTIONS: Adults & children above 12 years: 10 drops orally 3 times daily, or as directed by a health care professional.

KEEP OUT OF REACH OF CHILDREN

KEEP OUT OF THE REACH OF CHILDREN. In case of overdose (or accidental ingestion) get medical help or contact a Poison Control Center right away.

WARNINGS:

- IF PREGNANT OR BREAST-FEEDING, ask a health care professional before use.
- KEEP OUT OF THE REACH OF CHILDREN. In case of overdose (or accidental ingestion) get medical help or contact a Poison Control Center right away.
- Do not use if TAMPER EVIDENT seal is broken or missing.

INACTIVE INGREDIENT

INACTIVE INGREDIENTS: Citric Acid, Glycerin USP, Natural Cherry Flavor, Potassium Sorbate, Purified Water.

QUESTIONS & COMMENTS?

Natural Creations, Inc. / Woodbine, IA 51579 / 712-647-1600

REFERENCES

**Claims based on traditional homeopathic practice, not accepted medical evidence. Not FDA evaluated.

PACKAGE LABEL

NDC:43406-0133-1

Vaccine Support CP

HOMEOPATHIC

1 fl oz (30mL) / Alcohol Free

Natural Cherry Flavor